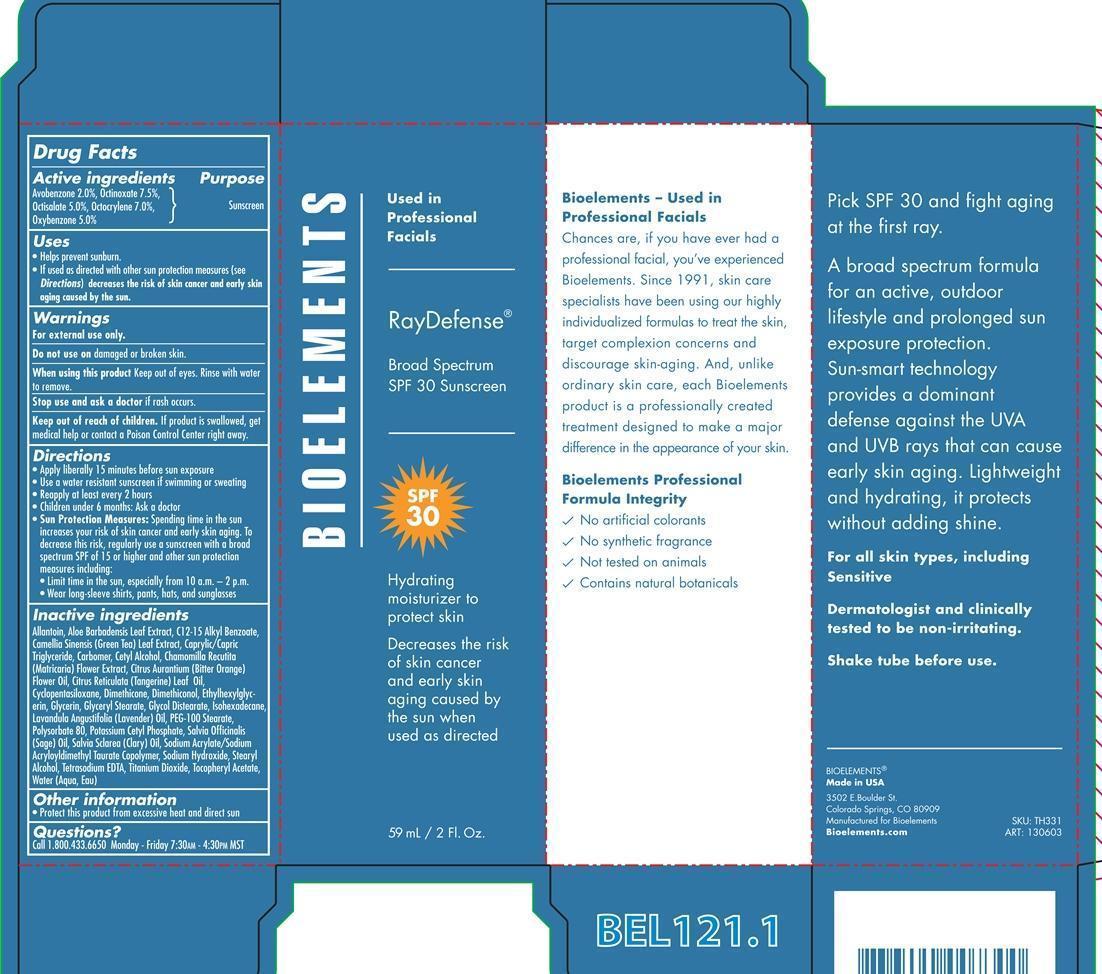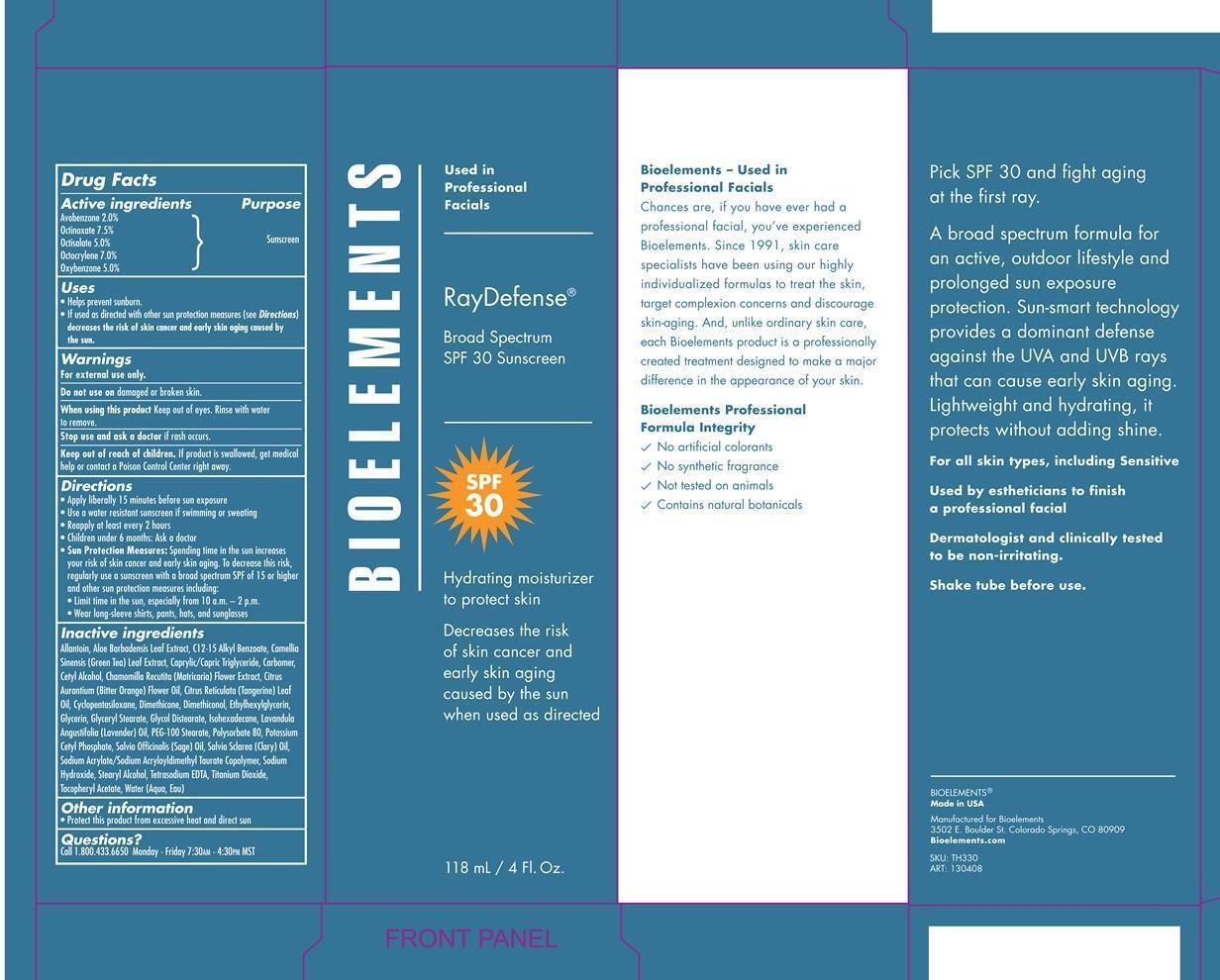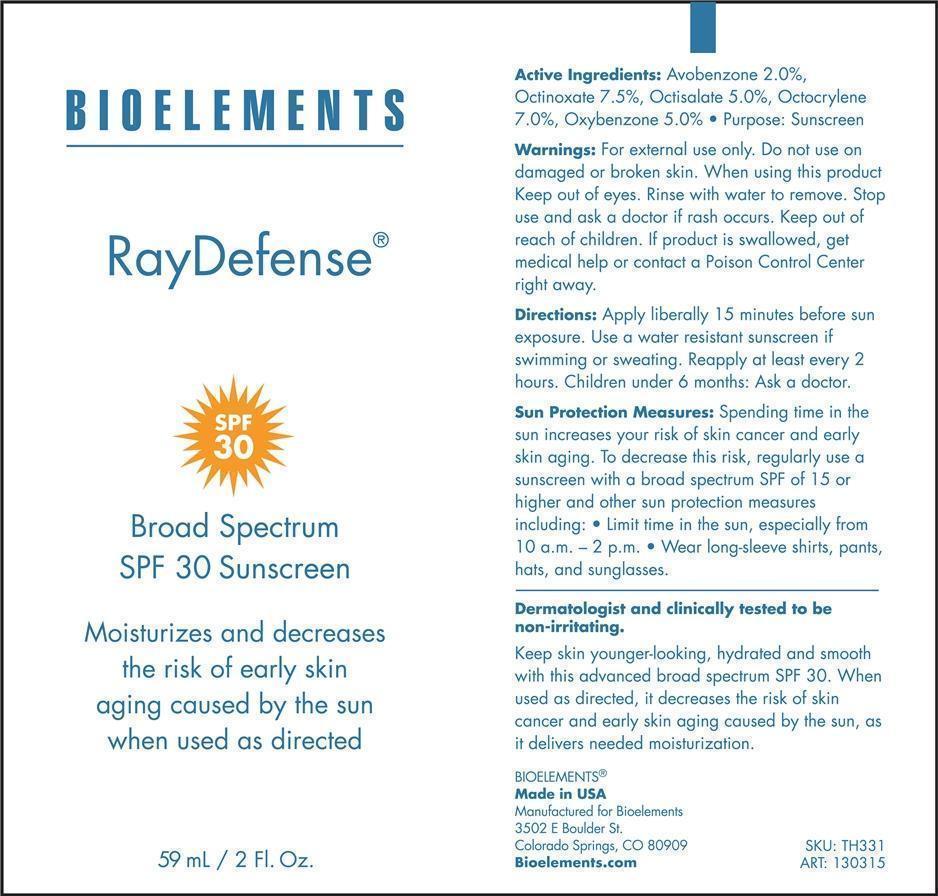 DRUG LABEL: Ray Defense Borad Spectrum SPF 30 sunscreen
NDC: 49825-132 | Form: CREAM
Manufacturer: Bioelements, Inc.
Category: otc | Type: HUMAN OTC DRUG LABEL
Date: 20130617

ACTIVE INGREDIENTS: AVOBENZONE 2 g/100 mL; OCTINOXATE 7.5 g/100 mL; OCTISALATE 5 g/100 mL; OCTOCRYLENE 7 g/100 mL; OXYBENZONE 5 g/100 mL
INACTIVE INGREDIENTS: ALLANTOIN; ALOE VERA LEAF; C12-15 ALKYL BENZOATE; GREEN TEA LEAF; MEDIUM-CHAIN TRIGLYCERIDES; CARBOMER 934; CETYL ALCOHOL; CHAMOMILE; CITRUS AURANTIUM FLOWER OIL; CITRUS RETICULATA LEAF OIL; CYCLOMETHICONE 5; DIMETHICONE; DIMETHICONOL (40 CST); ETHYLHEXYLGLYCERIN; GLYCERIN; GLYCERYL MONOSTEARATE; GLYCOL DISTEARATE; ISOHEXADECANE; LAVENDER OIL; PEG-100 STEARATE; POLYSORBATE 80; POTASSIUM CETYL PHOSPHATE; SAGE OIL; CLARY SAGE OIL; SODIUM ACRYLATE/SODIUM ACRYLOYLDIMETHYLTAURATE COPOLYMER (4000000 MW); SODIUM HYDROXIDE; STEARYL ALCOHOL; EDETATE SODIUM; TITANIUM DIOXIDE; .ALPHA.-TOCOPHEROL ACETATE; WATER

Ray Defense SPF 30

Active ingredients Sunscreen

Avobenzone 2.0% Sunscreen

Octinoxate 7.5% Sunscreen

Octisalate 5.0% Sunscreen

Octocrylene 7.0% Sunscreen

Oxybenzone 5.0% Sunscreen

Uses
· helps prevent sunburn
· If used as directed with other sun protection measures (see Directions),
decreases the risk of skin cancer and early skin aging caused by the sun

Keep out of reach of children. If product is swallowed, get medical help or
contact a Poison Control Center right away.

Stop use and ask a doctor if rash occurs

Warnings

· For external use only
· Do not use on damaged or broken skin
· When using this product keep out of eyes. Rinse with water to remove.

Directions
· Apply liberally 15 minutes before sun exposure
· Reapply at least every 2 hours
· Use a water resistant sunscreen if swimming or sweating
· Children under 6 months: Ask a doctor

Sun Protection Measures. Spending time in the sun increases your risk of skin
cancer and early skin aging. To decrease this risk, regularly use a sunscreen
with broad spectrum SPF of 15 or higher and other sun protection measures
including:
· limit time in the sun, especially from 10 a.m. - 2 p.m.
· wear long-sleeve shirts, pants, hats, and sunglasses

INACTIVE INGREDIENT

Allantoin, Aloe Barbdadenesis Leaf Extract, C12-15 Alkyl Benzoate, Camellia Sinensis (Green Tea) Leaf Extract, Caprylic/Capric Triglyceride, Carbomer, Cetyl Alcohol, Chamomilla Recutita (Matricaria) Flower Extract, Citrus Aurantium (Bitter Orange) Flower Oil, Citrus Reticulata (Tangerine) Leaf Oil, Cyclopentasiloxane, Dimethicone, Dimethiconol, Ethylhexylglycerin, Glycerin, Glyceryl Stearate, Glycol Distearate Isohexadecane, Lavandula Angustifolia (Lavender) Oil, PEG-100 Stearate, Polysorbate 80, Potassium Cetyl Phosphate, Salvia Officinalis (Sage) Oil, Salvia Sclarea (Clary) Oil, Sodium Acrylate/Sodium Acryloyldimethyl Taurate Copolymer, Sodium Hydroxide, Stearyl Alcohol, Tetrasodium EDTA, Titanium Dioxide, Tocopheryl Acetate, Water (Aqua, Eau).

PACKAGE LABEL

Bioelements

Ray defense Broad Spectrum SPF 30 Sunscreen

Hydrating moisturizer to protect skin

Decreases the risk of Skin Cancer and early skin aging caused by the sun when used as directed